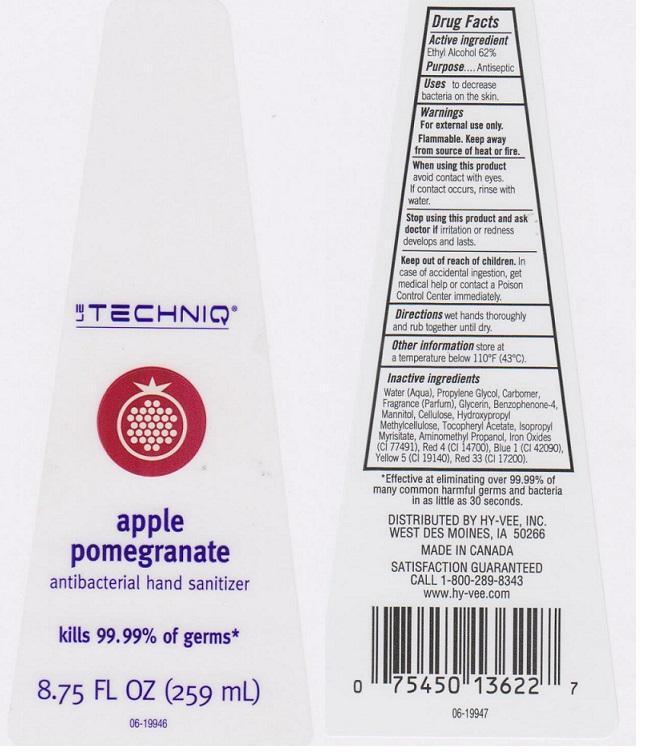 DRUG LABEL: LE TECHNIQ
NDC: 42507-262 | Form: LIQUID
Manufacturer: HYVEE INC
Category: otc | Type: HUMAN OTC DRUG LABEL
Date: 20141117

ACTIVE INGREDIENTS: ALCOHOL 620 mg/1 mL
INACTIVE INGREDIENTS: WATER; PROPYLENE GLYCOL; CARBOMER 934; GLYCERIN; SULISOBENZONE; MANNITOL; POWDERED CELLULOSE; HYPROMELLOSES; .ALPHA.-TOCOPHEROL ACETATE; ISOPROPYL MYRISTATE; AMINOMETHYLPROPANOL; FD&C BLUE NO. 1; FD&C YELLOW NO. 5; FERRIC OXIDE RED; FD&C RED NO. 4; D&C RED NO. 33

DRUG FACTS

ACTIVE INGREDIENT

ETHYL ALCOHOL 62%

PURPOSE

ANTISEPTIC

USES

TO DECREASE BACTERIA ON THE SKIN

WARNINGS

FOR EXTERNAL USE ONLY. FLAMMABLE. KEEP AWAY FROM SOURCE OF HEAT OR FIRE

WHEN USING THIS PRODUCT

AVOID CONTACT WITH EYES. IF CONTACT OCCURS, RINSE WITH WATER

STOP USING THIS PRODUCT AND ASK DOCTOR IF

IRRITATION OR REDNESS DEVELOPS AND LASTS

KEEP OUT OF REACH OF CHILDREN

IN CASE OF ACCIDENTAL INGESTION, GET MEDICAL HELP OR CONTACT A POISON CONTROL CENTER IMMEDIATELY

DIRECTIONS

WET HANDS THOROUGHLY AND RUB TOGETHER UNTIL DRY

OTHER INFORMATION

STORE AT A TEMPERATURE BELOW 110°F (43°C)

INACTIVE INGREDIENTS

WATER (AQUA), PROPYLENE GLYCOL, CARBOMER, FRAGRANCE (PARFUM), GLYCERIN, BENZOPHENONE-4, MANNITOL, CELLULOSE, HYDROXYPROPYL METHYLCELLULOSE, TOCOPHERYL ACETATE, ISOPROPYL MYRISTATE, AMINOMETHYL PROPANOL, IRON OXIDES (CI 77491), RED 4 (CI 14700), BLUE 1 (CI 42090), YELLOW 5 (CI 19140), RED 33 (CI 17200)